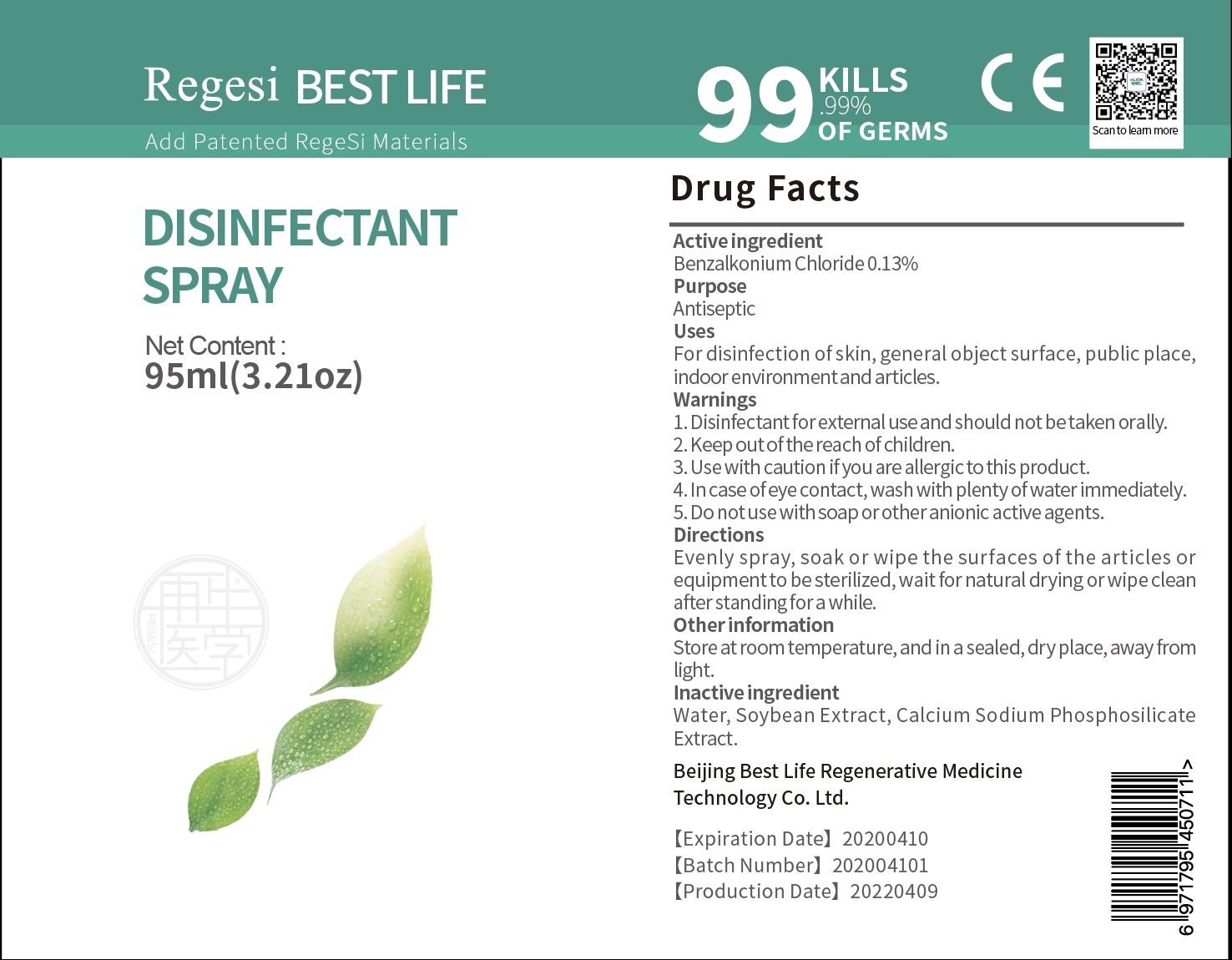 DRUG LABEL: Regisi Best Life Disinfectant Hand
NDC: 74684-001 | Form: SPRAY
Manufacturer: Beijing Best Life Regenerative Medicine Technology Co. Ltd.
Category: otc | Type: HUMAN OTC DRUG LABEL
Date: 20200408

ACTIVE INGREDIENTS: BENZALKONIUM CHLORIDE 0.13 g/100 mL
INACTIVE INGREDIENTS: CALCIUM SODIUM PHOSPHATE; WATER; SOYBEAN

Drug Fact

Active Ingredient(s)

BENZALKONIUM CHLORIDE: 0.13%

Purpose

Antiseptic

Use

For disinfection of skin, general object surface, public place, in door environment and articles

Warnings

Warning:

Disinfectant for eternal use and should not to be taken orally

Use with caution if you are allergic to this product

In the case of eye contact, wadh with plenty of water immediately

Do not use with soap or other anionic active agents

Keep out of reach of children.

Directions:

Evenly spray, soak, or wipe the surface of the article or euipment to be sterilized, wait for natural drying or wipe clean about atanding for a while

Inactive ingredients

Inactive Ingredients: Water, soybean exact, calcium sodium phosphosilicate extract

STORAGE AND HANDLING

Storage: Store at room temperature in a sealed dry place away from light